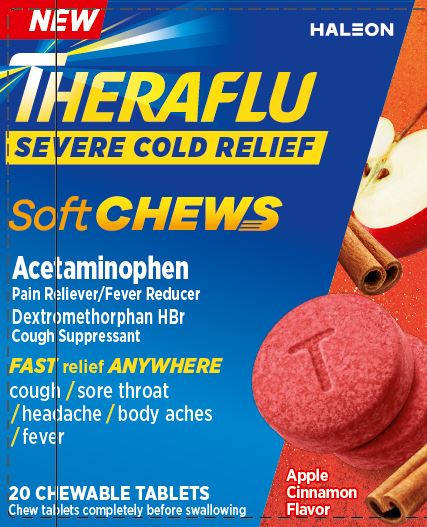 DRUG LABEL: Theraflu
NDC: 0067-0111 | Form: TABLET, CHEWABLE
Manufacturer: Haleon US Holdings LLC
Category: otc | Type: HUMAN OTC DRUG LABEL
Date: 20240619

ACTIVE INGREDIENTS: ACETAMINOPHEN 325 mg/1 1; DEXTROMETHORPHAN HYDROBROMIDE 10 mg/1 1
INACTIVE INGREDIENTS: CALCIUM GLUCONATE MONOHYDRATE; CARBOXYMETHYLCELLULOSE CALCIUM; CARNAUBA WAX; CORN SYRUP; CROSPOVIDONE, UNSPECIFIED; FD&C RED NO. 40; ALUMINUM OXIDE; FD&C YELLOW NO. 6; GLYCERIN; MANNITOL; STARCH, CORN; SODIUM GLUCONATE; SORBITOL; SORBITOL SOLUTION; SUCRALOSE; SUCROSE; COW MILK

Drug Facts

Active ingredients (in each chewable tablet)

Acetaminophen 325 mg

Dextromethorphan equivalent to 10 mg Dextromethorphan HBr

Purposes

Pain reliever/Fever reducer

Cough suppressant

Uses

- temporarily relieves these symptoms due to a cold:
  - minor aches and pains
  - sore throat pain
  - headache
  - cough due to minor throat and bronchial irritation
- temporarily reduces fever

Warnings

Liver warning: This product contains acetaminophen. Severe liver damage may occur if you take

- More than 4,000 mg of acetaminophen in 24 hours
- with other drugs containing acetaminophen
- 3 or more alcoholic drinks every day while using this product

Allergy alert: Acetaminophen may cause severe skin reactions. Symptoms may include:

- skin reddening
- blisters
- rash

If a skin reaction occurs, stop use and seek medical help right away.

Sore throat warning: If sore throat is severe, persists for more than 2 days, is accompanied or followed by fever, headache, rash, nausea, or vomiting consult a doctor promptly.

Do not use

- in a child under 12 years of age
- if you are allergic to acetaminophen
- with any other drug containing acetaminophen (prescription or nonprescription). If you are not sure whether a drug contains acetaminophen, ask a doctor or pharmacist.
- if you are now taking a prescription monoamine oxidase inhibitor (MAOI) (certain drugs for depression, psychiatric, or emotional conditions, or Parkinson’s disease), or for 2 weeks after stopping the MAOI drug. If you do not know if your prescription drug contains an MAOI, ask a doctor or pharmacist before taking this product.

Ask a doctor before use if you have

- liver disease
- cough that occurs with too much phlegm (mucus)
- cough that lasts or is chronic such as occurs with smoking, asthma or emphysema

Ask a doctor or pharmacist before use if you are

- taking the blood thinning drug warfarin

Stop use and ask a doctor if

- fever gets worse or lasts more than 3 days
- redness or swelling is present
- new symptoms occur
- pain or cough gets worse or lasts more than 7 days
- cough comes back or occurs with rash or headache that lasts

These could be signs of a serious condition.

If pregnant or breast-feeding,

ask a health professional before use.

Keep out of reach of children.

In case of overdose, get medical help or contact a Poison Control Center right away. Prompt medical attention is critical for adults as well as for children even if you do not notice any signs or symptoms.

Directions

- do not use more than directed
- do not take more than 10 chewable tablets in 24 hours unless directed by a doctor. Take every 4 hours, while symptoms persist.

Age | Dose
adults and children 12 years of age and over | take 2 chewable tablets every 4 hours
children under 12 years of age | do not use

Other information

- each chewable tablet contains: potassium 10 mg, sodium 6 mg
- store at a controlled room temperature 20-25°C (68-77°F)

Inactive ingredients

calcium gluconate monohydrate, carboxymethylcellulose calcium, carnauba wax, corn syrup solids, crospovidone, FD&C red no. 40 aluminum lake, FD&C yellow no. 6 aluminum lake, glycerin, mannitol, natural and artificial flavors, pregelatinized starch, simethicone, sodium gluconate, sorbitol, sorbitol solution, sucralose, sucrose, whole dry milk

Questions or comments?

call 1-855-328-5359

Generic Section

Do Not Use if seal under bottle cap imprinted with "SEALED for YOUR PROTECTION” is broken or missing.

Distributed by: Haleon, Warren, NJ 07059

Trademarks are owned by or licensed to the Haleon group of companies.

Pat. Info www.productpats.com

©2024 Haleon group of companies or its licensor.

PARENTS: Learn about teen medicine abuse. www.StopMedicineAbuse.org

211433

56047666

Peel Here

Package/Label Principal Display Panel

NEW

THERAFLU

SEVERE COLD RELIEF

SOFT CHEWS

Acetaminophen

Pain Reliever/Fever Reducer

Dextromethorphan HBr

Cough Suppressant

FAST relief ANYWHERE

cough / sore throat / headache / body aches / fever

20 CHEWABLE TABLETS

Chew tablets completely before swallowing

Apple Cinnamon Flavor